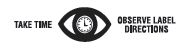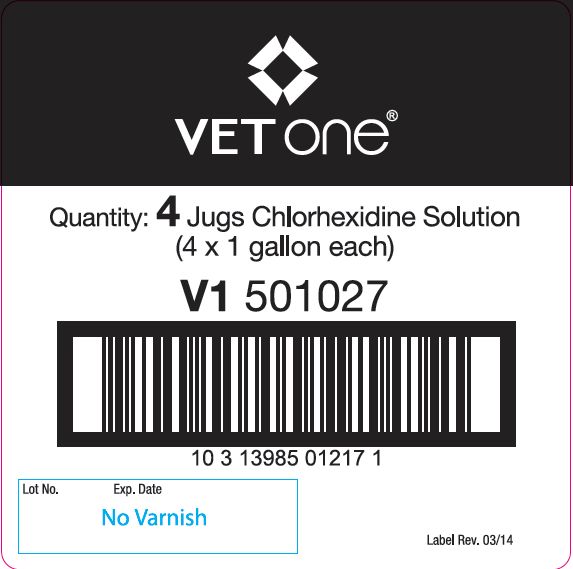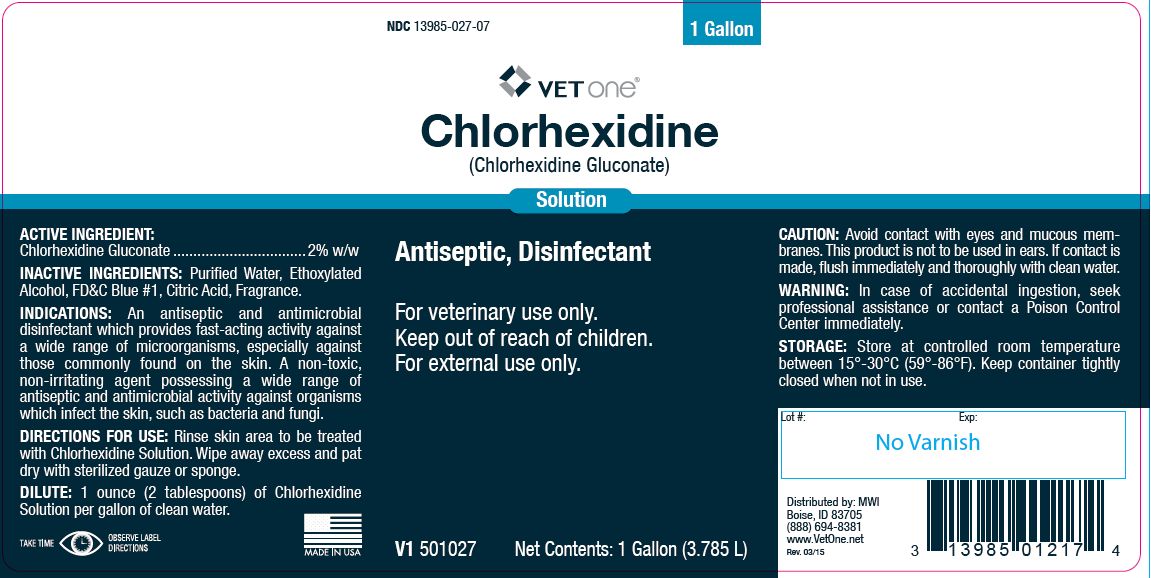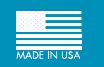 DRUG LABEL: CHLORHEXIDINE
NDC: 13985-027 | Form: SOLUTION
Manufacturer: MWI/Vet One
Category: animal | Type: OTC ANIMAL DRUG LABEL
Date: 20191016

ACTIVE INGREDIENTS: CHLORHEXIDINE GLUCONATE 99.0 g/1 L

Chlorhexidine

INFORMATION FOR OWNERS/CAREGIVERS

(Chlorhexidine Gluconate)

Solution

PURPOSE

Antiseptic, Disinfectant

KEEP OUT OF REACH OF CHILDREN

For veterinary use only.
Keep out of reach of children.
For external use only.

ACTIVE INGREDIENT:

Chlorhexidine Gluconate .................................2% w/w

INACTIVE INGREDIENTS:

Purified Water, Ethoxylated Alcohol, FD&C Blue #1, Citric Acid, Fragrance.

INDICATIONS:

An antiseptic and antimicrobial disinfectant which provides fast-acting activity against a wide range of microorganisms, especially against those commonly found on the skin. A non-toxic, non-irritating agent possessing a wide range of antiseptic and antimicrobial activity against organisms which infect the skin, such as bacteria and fungi.

DIRECTIONS FOR USE:

Rinse skin area to be treated with Chlorhexidine Solution. Wipe away excess and pat dry with sterilized gauze or sponge.

DILUTE:

1 ounce (2 tablespoons) of Chlorhexidine Solution per gallon of clean water.

CAUTION:

Avoid contact with eyes and mucous membranes. This product is not to be used in ears. If contact is made, flush immediately and thoroughly with clean water.

WARNING:

In case of accidental ingestion, seek professional assistance or contact a Poison Control Center immediately.

STORAGE:

Store at controlled room temperature between 15°-30°C (59°-86°F). Keep container tightly closed when not in use.

Net Contents:

One Gallon (3.785 L) V1 501027

INFORMATION FOR OWNERS/CAREGIVERS

Distributed by: MWI
Boise, ID 83705
(888) 694-8381
www.VetOne.net
Rev. 03/15